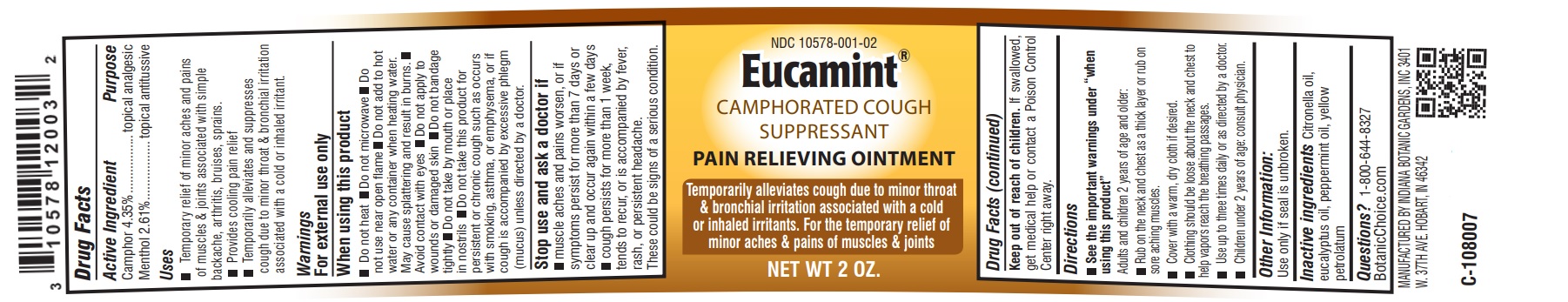 DRUG LABEL: Eucamint
NDC: 10578-001 | Form: OINTMENT
Manufacturer: Indiana Botanic Gardens
Category: otc | Type: HUMAN OTC DRUG LABEL
Date: 20241213

ACTIVE INGREDIENTS: MENTHOL 2.61 g/100 g; CAMPHOR (SYNTHETIC) 4.35 g/100 g
INACTIVE INGREDIENTS: PETROLATUM; EUCALYPTUS OIL; PEPPERMINT OIL; CITRONELLA OIL

Eucamint

Active Ingredient

Camphor 4.35%

Menthol 2.61%

Purpose

topical analgesic

topical antitussive

Uses

Temporary relief of minor aches and pains of muscles & joints associated with simple backache, arthritis, bruises, sprains

Provides cooling pain relief

Temporarily alleviates and suppresses cough due to minor throat & bronchial irritation associated with a cold or inhaled irritant.

Warnings:

For external use only

When using this product

Do not heat

Do not microwave

Do not add to hot water or any container when heating water. May cause splattering and result in burns.

Avoid contact with eyes

Do not apply to wounds or damaged skin

Do not bandage tightly

Do not take by mouth or place in nostrils

Do not take or give this product for persistent or chronic cough such as occurs with asthma or if cough is accompanied by excessive phlegm (mucous) unless directed by a doctor.

Stop use and ask a doctor if

muscle aches and pains worsen, or if symptoms persist for more than 7 days or clear up and occur again within a few days

cough persists for more than 1 week, tends to recur, or is accompanied by fever, rash, or persistent headache.

These could be signs of a serious condition.

Keep out of reach of children.

If swallowed, get medical help or contact a Poison Control Center right away.

Directions

See the important warnings under "when using this product"

Adults and children 2 years of age and older:

Rub on the neck and chest as a thick layer or rub on sore aching muscles.

Cover with a warm, dry cloth if desired.

Clothing should be loose about the neck and chest to help vapors reach the breathing passages.

Use up to three times daily or as directed by a doctor.

Children under 2 years of age: consult physician.

Other Information:

Use only if seal is unbroken.

Inactive Ingredients

Citronella oil, eucalyptus oil, peppermint oil, yellow petrolatum

Questions?

1-800-644-8327

BotanicChoice.com

Manufactured by Indiana Botanic Gardens, Inc

3401 W. 37th Ave. Hobart, IN 46342

C-108007

PACKAGE LABEL

NDC 10578-001-02

Eucamint(r)

Camphorated Cough

Suppressant

Pain Relieving Ointment

Temporarily alleviates cough due to minor throat & bronchial irritation associated with a cold or inhaled irritants. For the temporary relief of minor aches & pains of muscles & joints

Net Wt 2 oz.